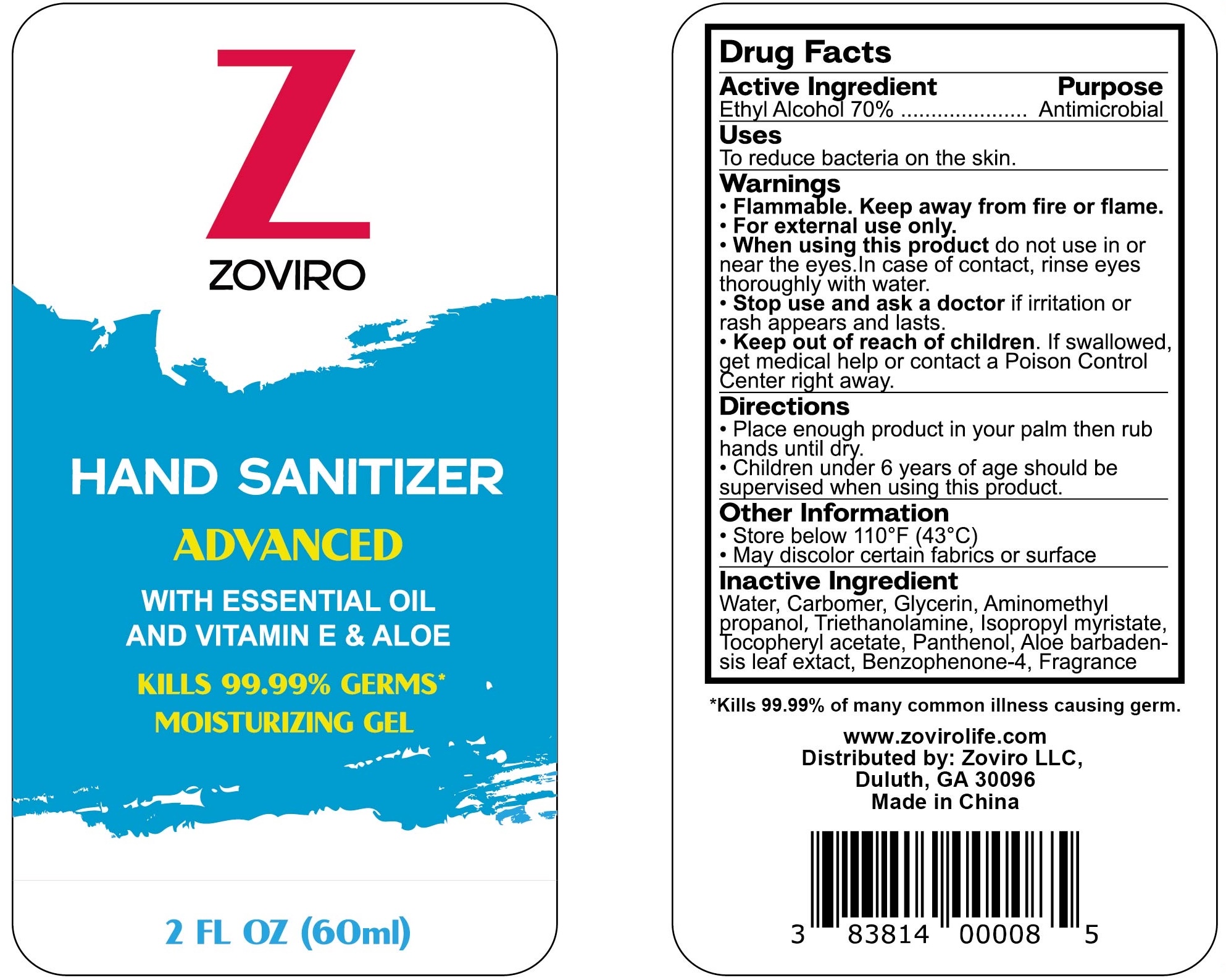 DRUG LABEL: Zoviro
NDC: 83814-005 | Form: LIQUID
Manufacturer: Zoviro, LLC
Category: otc | Type: HUMAN OTC DRUG LABEL
Date: 20251006

ACTIVE INGREDIENTS: ALCOHOL 70 mL/100 mL
INACTIVE INGREDIENTS: PANTHENOL; ALOE VERA LEAF; SULISOBENZONE; ISOPROPYL MYRISTATE; WATER; CARBOMER 1342; GLYCERIN; .ALPHA.-TOCOPHEROL ACETATE; AMINOMETHYLPROPANOL; TROLAMINE

Zoviro Hand Sanitizer Soothing Gel, Refreshing Scent, Advanced Formula, 2 fl oz Travel Size Flip-Cap Bottle

Active Ingredient

Ethyl Alcohol 70%

Purpose

Antimicrobial

Inactive Ingredient

Water, Carbomer, Glycerin, Aminomethyl propanol, Triethanolamine, Isopropyl myristate, locopheryl acetate, Panthenol, Aloe barbaden-sis leaf extact, Benzophenone-4, Fragrance

Stop use and ask a doctor if irritation or rash appears and lasts.

Warnings

Flammable. Keep away from fire or flame.

For external use only.

When using this product do not use in or near the eyes. In case of contact, rinse eyes thoroughly with water.

Keep out of reach of children. If swallowed, get medical help or contact a Poison Control Center right away.

Directions
Place enough product in your palm then rub hands until dry.
Children under 6 years of age should be supervised when using this product.

Uses

To reduce bacteria on the skin.